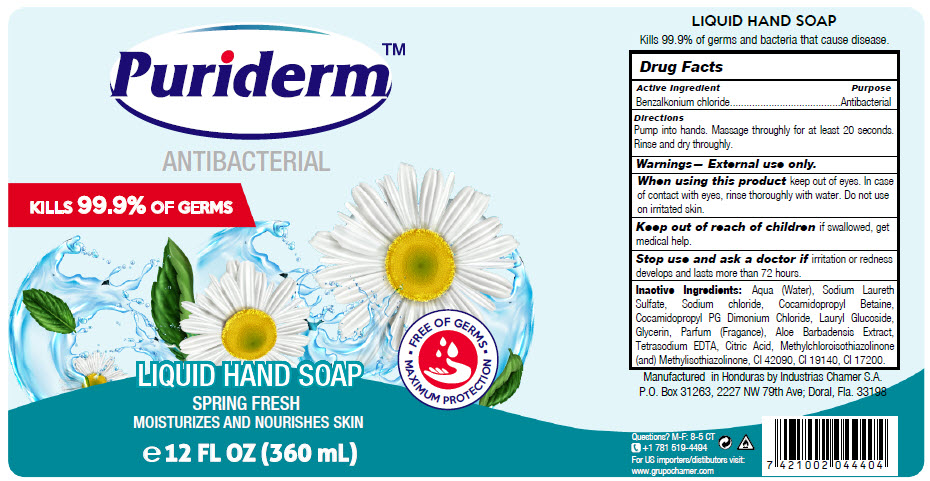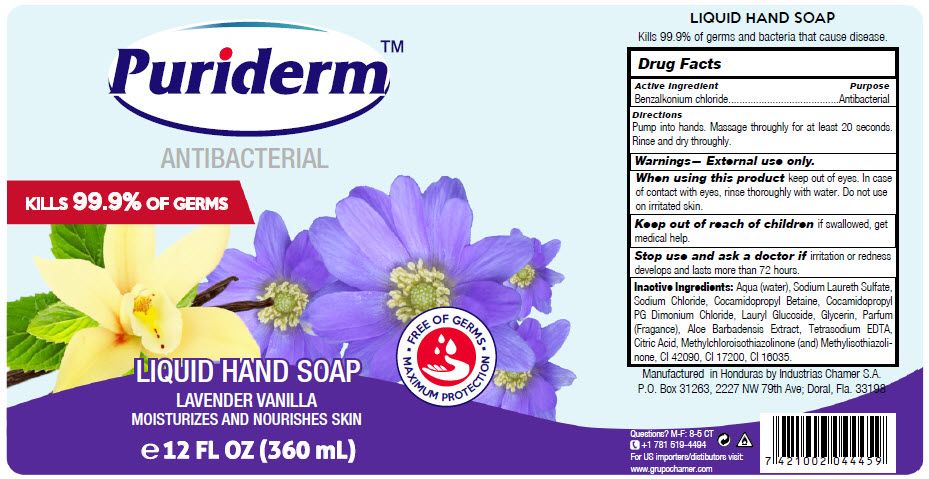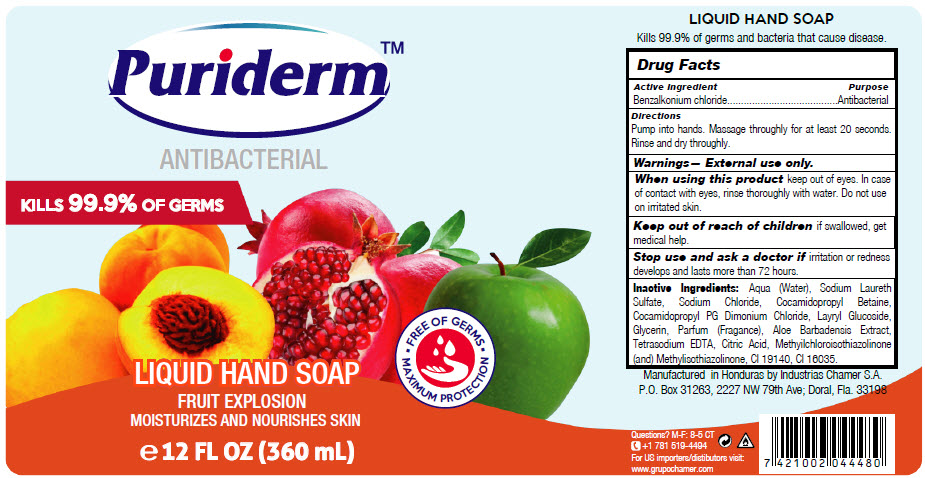 DRUG LABEL: PURIDERM 
NDC: 51774-002 | Form: LIQUID
Manufacturer: INDUSTRIAS CHAMER S.A. DE C.V.
Category: otc | Type: HUMAN OTC DRUG LABEL
Date: 20200806

ACTIVE INGREDIENTS: BENZALKONIUM CHLORIDE 1 mg/1 mL
INACTIVE INGREDIENTS: COCAMIDOPROPYL PROPYLENE GLYCOL-DIMONIUM CHLORIDE PHOSPHATE 7.5 mg/1 mL; WATER; SODIUM LAURETH-3 SULFATE; SODIUM CHLORIDE; COCAMIDOPROPYL BETAINE; LAURYL GLUCOSIDE; GLYCERIN; ALOE VERA LEAF; EDETATE SODIUM; CITRIC ACID MONOHYDRATE; METHYLCHLOROISOTHIAZOLINONE; FD&C BLUE NO. 1; FD&C YELLOW NO. 5; D&C RED NO. 33

PURIDERM™
ANTIBACTERIAL

Drug Facts

Active Ingredient

Benzalkonium chloride

Purpose

Antibacterial

INDICATIONS AND USAGE

Directions

Pump into hands. Massage throughly for at least 20 seconds. Rinse and dry throughly.

Warnings

External use only.

When using this product keep out of eyes. In case of contact with eyes, rinse thoroughly with water. Do not use on irritated skin.

Keep out of reach of children if swallowed, get medical help.

Stop use and ask a doctor if irritation or redness develops and lasts more than 72 hours.

Inactive Ingredients

Aqua (Water), Sodium Laureth Sulfate, Sodium chloride, Cocamidopropyl Betaine, Cocamidopropyl PG Dimonium Chloride, Lauryl Glucoside, Glycerin, Parfum (Fragance), Aloe Barbadensis Extract, Tetrasodium EDTA, Citric Acid, Methylchloroisothiazolinone (and) Methylisothiazolinone, CI 42090, CI 19140, CI 17200.

Questions?

M-F: 8-5 CT

+1 781 519-4494

PRINCIPAL DISPLAY PANEL - 360 mL Bottle Label - Spring Fresh

Puriderm™

ANTIBACTERIAL

KILLS 99.9% OF GERMS

LIQUID HAND SOAP

SPRING FRESH
MOISTURIZES AND NOURISHES SKIN

FREE OF GERMS
MAXIMUM PROTECTION

℮ 12 FL OZ (360 mL)

PRINCIPAL DISPLAY PANEL - 360 mL Bottle Label - Lavender Vanilla

Puriderm™

ANTIBACTERIAL

KILLS 99.9% OF GERMS

LIQUID HAND SOAP

LAVENDER VANILLA
MOISTURIZES AND NOURISHES SKIN

FREE OF GERMS
MAXIMUM PROTECTION

℮ 12 FL OZ (360 mL)

PRINCIPAL DISPLAY PANEL - 360 mL Bottle Label - Fruit Explosion

Puriderm™

ANTIBACTERIAL

KILLS 99.9% OF GERMS

LIQUID HAND SOAP

FRUIT EXPLOSION
MOISTURIZES AND NOURISHES SKIN

FREE OF GERMS
MAXIMUM PROTECTION

℮ 12 FL OZ (360 mL)